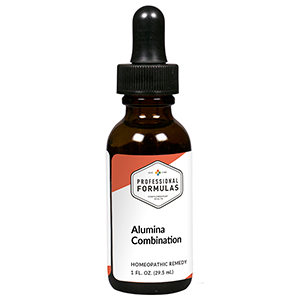 DRUG LABEL: Alumina Combination
NDC: 63083-9204 | Form: LIQUID
Manufacturer: Professional Complementary Health Formulas
Category: homeopathic | Type: HUMAN OTC DRUG LABEL
Date: 20190815

ACTIVE INGREDIENTS: SAW PALMETTO 2 [hp_X]/29.5 mL; BERBERIS VULGARIS ROOT BARK 3 [hp_X]/29.5 mL; CHONDRODENDRON TOMENTOSUM ROOT 3 [hp_X]/29.5 mL; LYTTA VESICATORIA 4 [hp_X]/29.5 mL; CAUSTICUM 4 [hp_X]/29.5 mL; NITRIC ACID 6 [hp_X]/29.5 mL; ALUMINUM OXIDE 12 [hp_X]/29.5 mL; LEAD 12 [hp_X]/29.5 mL
INACTIVE INGREDIENTS: ALCOHOL; WATER

R204

ACTIVE INGREDIENTS

Sabal serrulata 2X
Berberis vulgaris 3X
Pareira brava 3X
Cantharis 4X
Causticum 4X
Nitricum acidum 6X
Alumina 12X
Plumbum aceticum 12X

QUESTIONS

Professional Formulas

PO Box 2034 Lake Oswego, OR 97035

INDICATIONS

For the temporary relief of constipation, mild abdominal pain, or urinary discomfort.*

PURPOSE

*Claims based on traditional homeopathic practice, not accepted medical evidence. Not FDA evaluated.

WARNINGS

Consult a doctor if condition worsens, if symptoms persist, or are accompanied by fever, vomiting, or bloody or cloudy urine. Keep out of the reach of children. In case of overdose, get medical help or contact a poison control center right away. If pregnant or breastfeeding, ask a healthcare professional before use.

Keep out of the reach of children.

PREGNANCY OR BREAST FEEDING

If pregnant or breastfeeding, ask a healthcare professional before use.

DIRECTIONS

Place drops under tongue 30 minutes before/after meals. Adults and children 12 years and over: Take 10 drops up to 3 times per day. Consult a physician for use in children under 12 years of age.

OTHER INFORMATION

Tamper resistant. If seal is broken, do not use. After opening, close container tightly and store at room temperature away from heat.

INACTIVE INGREDIENTS

40% ethanol, purified water.

LABEL

Est 1985

Professional Formulas

Complementary Health

Alumina Combination

Homeopathic Remedy

1 FL. OZ. (29.5 mL)